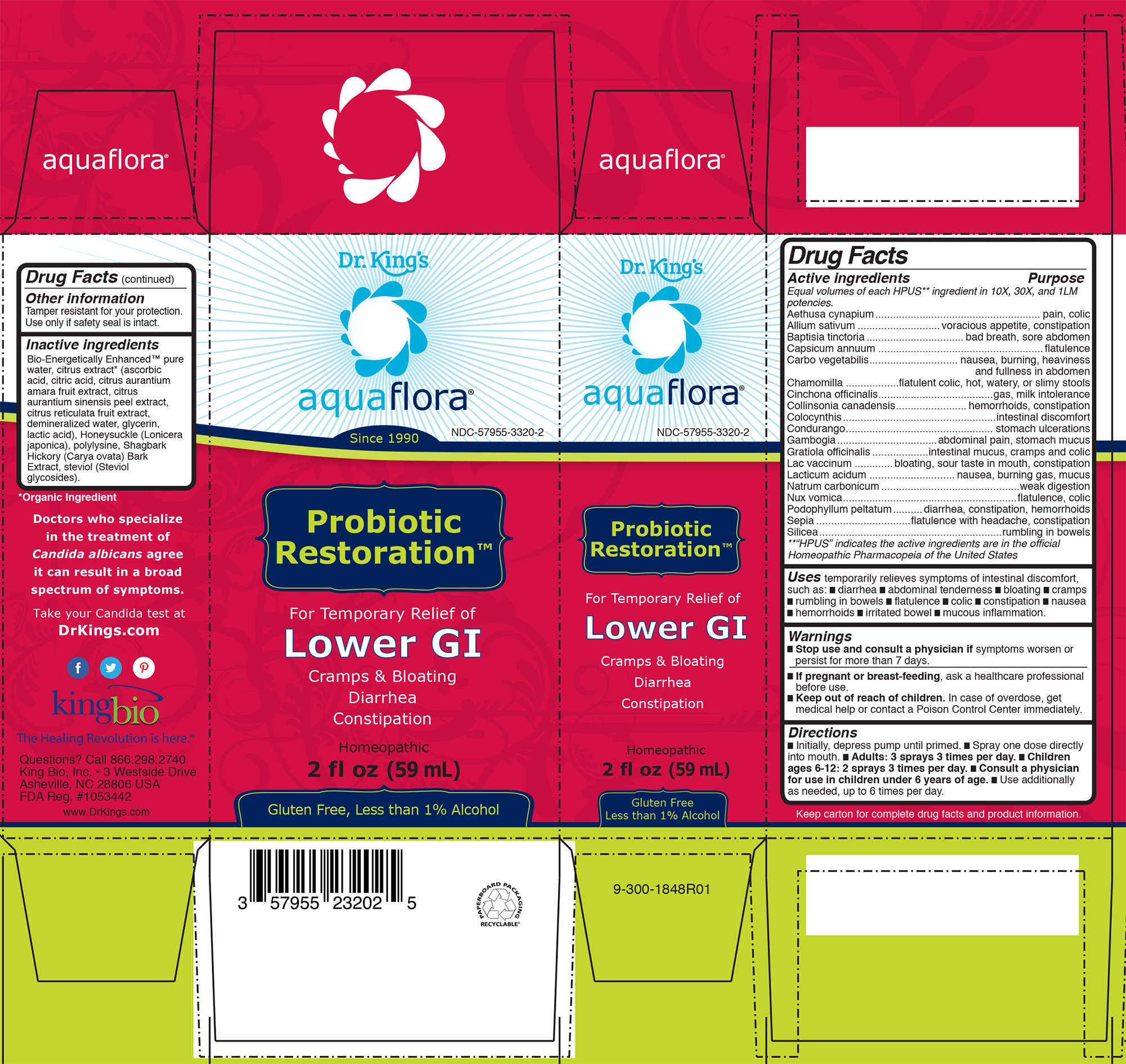 DRUG LABEL: Probiotic Restoration
NDC: 57955-3320 | Form: LIQUID
Manufacturer: King Bio Inc.
Category: homeopathic | Type: HUMAN OTC DRUG LABEL
Date: 20201012

ACTIVE INGREDIENTS: AETHUSA CYNAPIUM 10 [hp_X]/59 mL; GARLIC 10 [hp_X]/59 mL; BAPTISIA TINCTORIA ROOT 10 [hp_X]/59 mL; CAPSICUM 10 [hp_X]/59 mL; ACTIVATED CHARCOAL 10 [hp_X]/59 mL; MATRICARIA RECUTITA 10 [hp_X]/59 mL; CINCHONA OFFICINALIS BARK 10 [hp_X]/59 mL; COLLINSONIA CANADENSIS ROOT 10 [hp_X]/59 mL; CITRULLUS COLOCYNTHIS FRUIT PULP 10 [hp_X]/59 mL; MARSDENIA CONDURANGO BARK 10 [hp_X]/59 mL; GAMBOGE 10 [hp_X]/59 mL; GRATIOLA OFFICINALIS 10 [hp_X]/59 mL; COW MILK 10 [hp_X]/59 mL; LACTIC ACID, DL- 10 [hp_X]/59 mL; SODIUM CARBONATE 10 [hp_X]/59 mL; STRYCHNOS NUX-VOMICA SEED 10 [hp_X]/59 mL; PODOPHYLLUM 10 [hp_X]/59 mL; SEPIA OFFICINALIS JUICE 10 [hp_X]/59 mL; SILICON DIOXIDE 10 [hp_X]/59 mL
INACTIVE INGREDIENTS: WATER; CARYA OVATA BARK; CITRUS BIOFLAVONOIDS; LONICERA JAPONICA FLOWER; POLYEPSILON-LYSINE (4000 MW); REBAUDIOSIDE A

Probiotic Restoration

Drug Facts

_____________________________________________________________________________________________________________________

HPUS active ingredients

Aethusa cynapium, Allium sativum, Baptisia tinctoria, Capsicum annuum, Carbo vegetabilis, Chamomilla, Cinchona officinalis, Collinsonia canadensis, Colcynthis, Condurango, Gambogia, Gratiola officinalis, Lac vaccinum, Lacticum acidum, Natrum carbonicum, Nux vomica, Podophyllum peltatum, Sepia, Silicea.

INDICATIONS AND USAGE

Uses temporarily relieves symptoms of intestinal discomfort,
such as: █ diarrhea █ abdominal tenderness █ bloating █ cramps
█ rumbling in bowels █ flatulence █ colic █ constipation █ nausea
█ hemorrhoids █ irritated bowel █ mucous inflammation.

Warnings

█ Stop use and consult a physician if symptoms worsen or
persist for more than 7 days

PREGNANCY OR BREAST FEEDING

█ If pregnant or breast-feeding, ask a healthcare professional
before use.

█ Keep out of reach of children. In case of overdose, get
medical help or contact a Poison Control Center immediately.

Directions
█ Initially, depress pump until primed. █ Spray one dose directly
into mouth. █ Adults: 3 sprays 3 times per day. █ Children
ages 6-12: 2 sprays 3 times per day. █ Consult a physician
for use in children under 6 years of age. █ Use additionally
as needed, up to 6 times per day.

INDICATIONS AND USAGE

Uses temporarily relieves symptoms of intestinal discomfort,
such as: █ diarrhea █ abdominal tenderness █ bloating █ cramps
█ rumbling in bowels █ flatulence █ colic █ constipation █ nausea
█ hemorrhoids █ irritated bowel █ mucous inflammation.

Other information

Tamper resistant for your protection. Use only if safety seal is intact.

Inactive ingredients

Bio-Energetically Enhanced™ pure
water, citrus extract* (ascorbic
acid, citric acid, citrus aurantium
amara fruit extract, citrus
aurantium sinensis peel extract,
citrus reticulata fruit extract,
demineralized water, glycerin,
lactic acid), Honeysuckle (Lonicera
japonica), polylysine, Shagbark
Hickory (Carya ovata) Bark
Extract, steviol (Steviol
glycosides).

Drug Facts

Active ingredients ........................................................... Purpose

Equal volumes of each HPUS** ingredient in 10X, 30X, and 1LM
potencies.

Aethusa cynapium........................................................ pain, colic
Allium sativum ............................voracious appetite, constipation
Baptisia tinctoria.................................bad breath, sore abdomen
Capsicum annuum ........................................................flatulence
Carbo vegetabilis.............................. nausea, burning, heaviness
and fullness in abdomen
Chamomilla ..................flatulent colic, hot, watery, or slimy stools
Cinchona officinalis.......................................gas, milk intolerance
Collinsonia canadensis........................ hemorrhoids, constipation
Colocynthis....................................................intestinal discomfort
Condurango.................................................. stomach ulcerations
Gambogia..................................abdominal pain, stomach mucus
Gratiola officinalis...................intestinal mucus, cramps and colic
Lac vaccinum .............bloating, sour taste in mouth, constipation
Lacticum acidum .............................nausea, burning gas, mucus
Natrum carbonicum...............................................weak digestion
Nux vomica...........................................................flatulence, colic
Podophyllum peltatum..........diarrhea, constipation, hemorrhoids
Sepia ................................flatulence with headache, constipation
Silicea..............................................................rumbling in bowels

**“HPUS” indicates the active ingredients are in the official
Homeopathic Pharmacopeia of the United States

Questions? Call 866.298.2740
King Bio, Inc. • 3 Westside Drive
Asheville, NC 28806 USA
FDA Reg. #1053442

www.DrKings.com

Other information
Tamper resistant for your protection.
Use only if safety seal is intact.